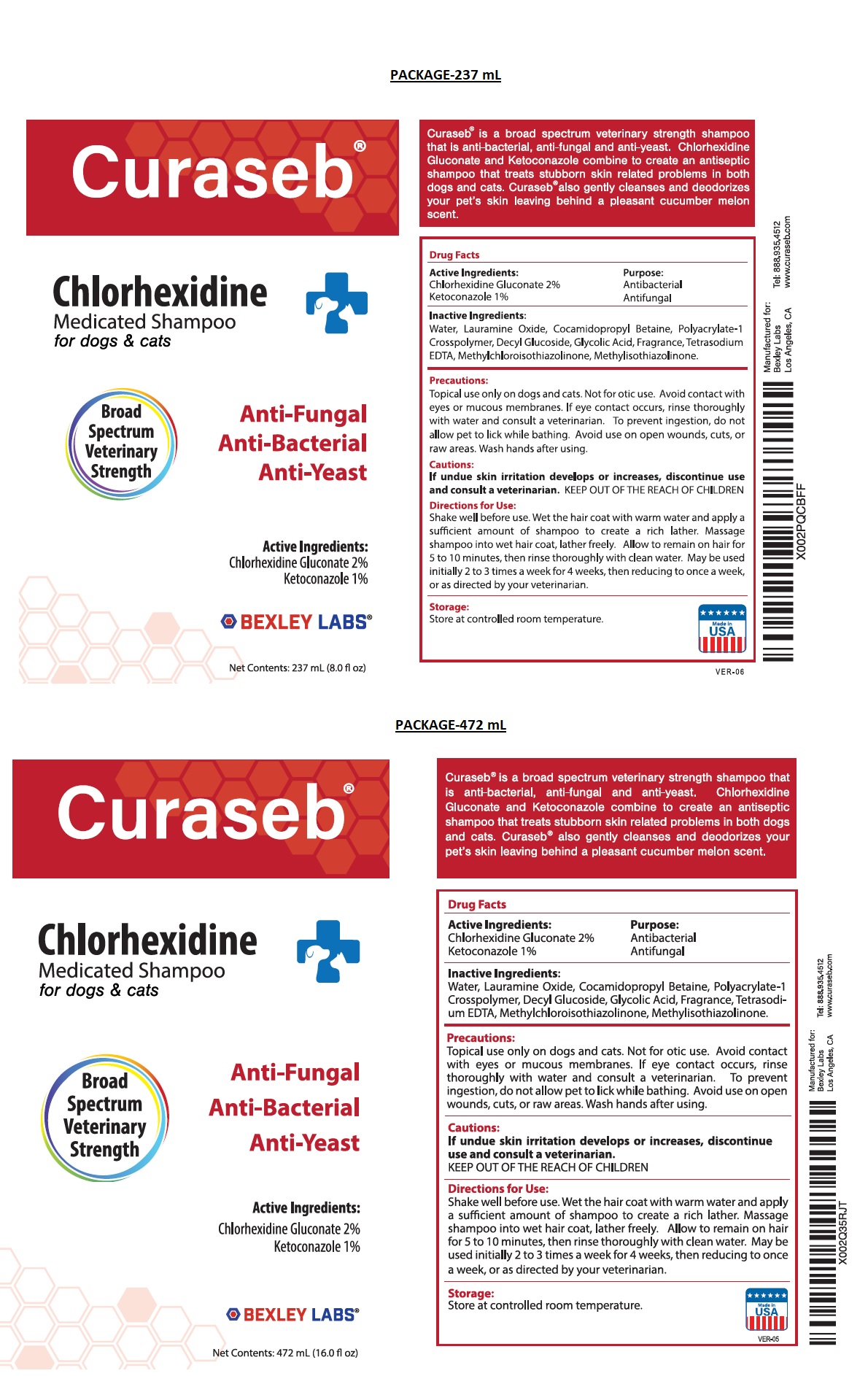 DRUG LABEL: Curaseb
NDC: 86133-102 | Form: SHAMPOO
Manufacturer: Bexley Labs
Category: animal | Type: OTC ANIMAL DRUG LABEL
Date: 20230223

ACTIVE INGREDIENTS: CHLORHEXIDINE GLUCONATE 2 g/100 mL; KETOCONAZOLE 1 g/100 mL
INACTIVE INGREDIENTS: WATER; LAURAMINE OXIDE; COCAMIDOPROPYL BETAINE; POLYACRYLATE-1 CROSSPOLYMER; DECYL GLUCOSIDE; GLYCOLIC ACID; EDETATE SODIUM; METHYLCHLOROISOTHIAZOLINONE; METHYLISOTHIAZOLINONE

Curaseb® Chlorhexidine Medicated Shampoo

Active Ingredients:

Chlorhexidine Gluconate 2%
Ketoconazole 1%.

Purpose:

Antibacterial
Antifungal

INDICATIONS AND USAGE

Curaseb® is a broad spectrum veterinary strength shampoo that is anti-bacterial, anti-fungal and anti-yeast. Chlorexidine Gluconate and Ketoconazole combine to create an antiseptic shampoo that treats stubborn skin related problems in both dogs and cats. Curaseb® also gently cleanses and deodorizes your pets's skin leaving behind a pleasant cucumber melon scent.

Inactive Ingredients:

Water, Lauramine Oxide, Cocamidopropyl Betaine, Polyacrylate-1 Crosspolymer, Decyl Glucoside, Glycolic Acid, Fragrance, Tetrasodium EDTA, Methylchloroisothiazolinone, Methylisothiazolinone.

Precautions:

Topical use only on dogs and cats. Not for otic use. Avoid contact with eyes or mucous membranes. If eye contact occurs, rinse thoroughly with water and consult a veterinarian. To prevent ingestion, do not allow pet to lick while bathing. Avoid use on open wounds, cuts, or raw areas. Wash hands after using.

Cautions:

If undue skin irritation develops or increases, discontinue use and consult a veterinarian.

KEEP OUT OF THE REACH OF CHILDREN

Directions for Use:

Shake well before use. Wet the hair coat with warm water and apply a sufficient amount of shampoo to create a rich lather. Massage shampoo into wet hair coat, lather freely. Allow to remain on hair for 5 to 10 minutes, then rinse thoroughly with clean water. May be used initially 2 to 3 times a week for 4 weeks, then reducing to once a week, or as directed by your veterinarian.

Storage:

Store at controlled room temperature.

for dogs & cats

Made in USA

Manufactured for:
Bexley Labs
Los Angeles, CA

Tel:888.935.4512
www.curaseb.com